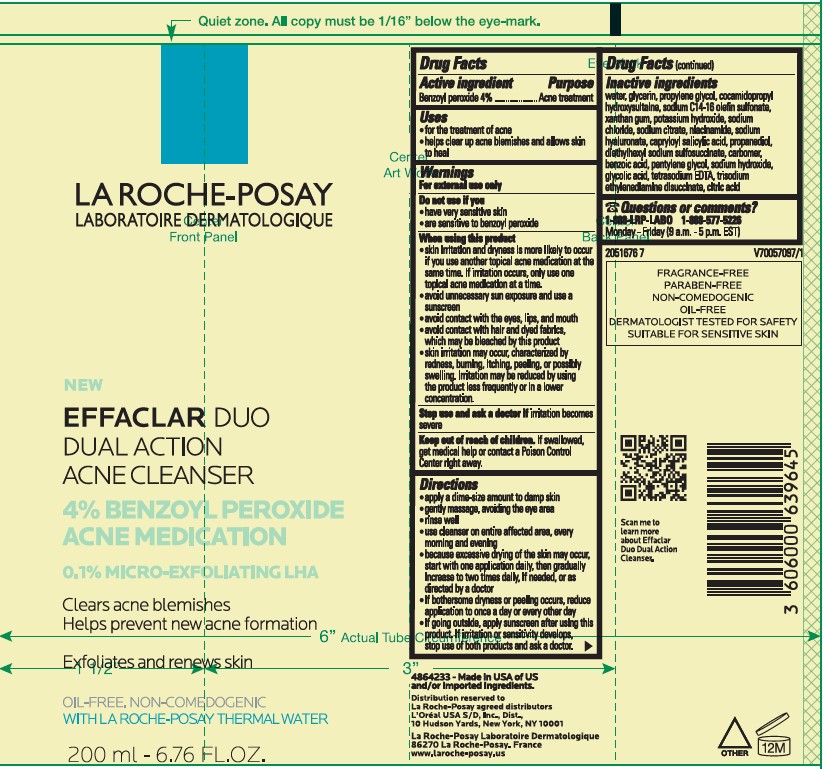 DRUG LABEL: La Roche Posay Laboratoire Dermatologique Effaclar Duo Dual Action Acne Medication Cleanser
NDC: 49967-647 | Form: LIQUID
Manufacturer: L'Oreal USA Products Inc
Category: otc | Type: HUMAN OTC DRUG LABEL
Date: 20250709

ACTIVE INGREDIENTS: Benzoyl peroxide 40 mg/1 mL
INACTIVE INGREDIENTS: WATER; GLYCERIN; PROPYLENE GLYCOL; COCAMIDOPROPYL HYDROXYSULTAINE; SODIUM C14-16 OLEFIN SULFONATE; XANTHAN GUM; POTASSIUM HYDROXIDE; SODIUM CHLORIDE; SODIUM CITRATE; NIACINAMIDE; SODIUM HYALURONATE; CAPRYLOYL SALICYLIC ACID; PROPANEDIOL; DIETHYLHEXYL SODIUM SULFOSUCCINATE; CARBOMER; BENZOIC ACID; PENTYLENE GLYCOL; SODIUM HYDROXIDE; GLYCOLIC ACID; TETRASODIUM EDTA; TRISODIUM ETHYLENEDIAMINE DISUCCINATE; CITRIC ACID

Drug Facts

Active ingredient

Benzoyl peroxide 4.0%

Purpose

Acne treatment

Uses

- for the treatment of acne
- helps clear up blemishes and allows skin to heal

Warnings

For external use only

Do not use if you

have very sensitive skin
are sensitive to benzoyl peroxide

When using this product

- skin irritation and dryness is more likely to occur if you use another topical acne medication at the same time. If irritation occurs, only use one topical acne medication at a time
- avoid unnecessary sun exposure and use a sunscreen
- avoid contact with the eyes, lips and mouth
- avoid contact with hair and dyed fabrics, which may be bleached by this product
- skin irritation may occur, characterized by redness, burning, itching, peeling, or possibly swelling. Irritation may be reduced by using the product less frequently or in a lower concentration.

Stop use and ask a doctor if

irritation becomes severe

Keep out of reach of children.

If swallowed, get medical help or contact a Poison Control Center right away.

Directions

• apply a dime-size amount to damp skin

• gently massage, avoiding the eye area

• rinse well

• use cleanser on entire affected area, every morning and evening

• because excessive drying of the skin may occur, start with one application daily, then gradually increase to two times daily, if needed, or as directed by a doctor

• if bothersome dryness or peeling occurs, reduce application to once a day or every other day

• if going outside, apply sunscreen after using this product • if irritation or sensitivity develops, stop use of both products and ask a doctor

Inactive ingredients

water, glycerin, propylene glycol, cocamidopropyl hydroxysultaine, sodium C14-16 olefin sulfonate, xanthan gum, potassium hydroxide, sodium chloride, sodium citrate, niacinamide, sodium hyaluronate, capryloyl salicylic acid, propanediol, diethylhexyl sodium sulfosuccinate, carbomer, benzoic acid, pentylene glycol, sodium hydroxide, glycolic acid, tetrasodium EDTA, trisodium ethylenediamine disuccinate, citric acid

Questions or comments?

1-888-LRP-LABO 1-888-577-5226

Monday - Friday (9 a.m. - 5 p.m. EST)